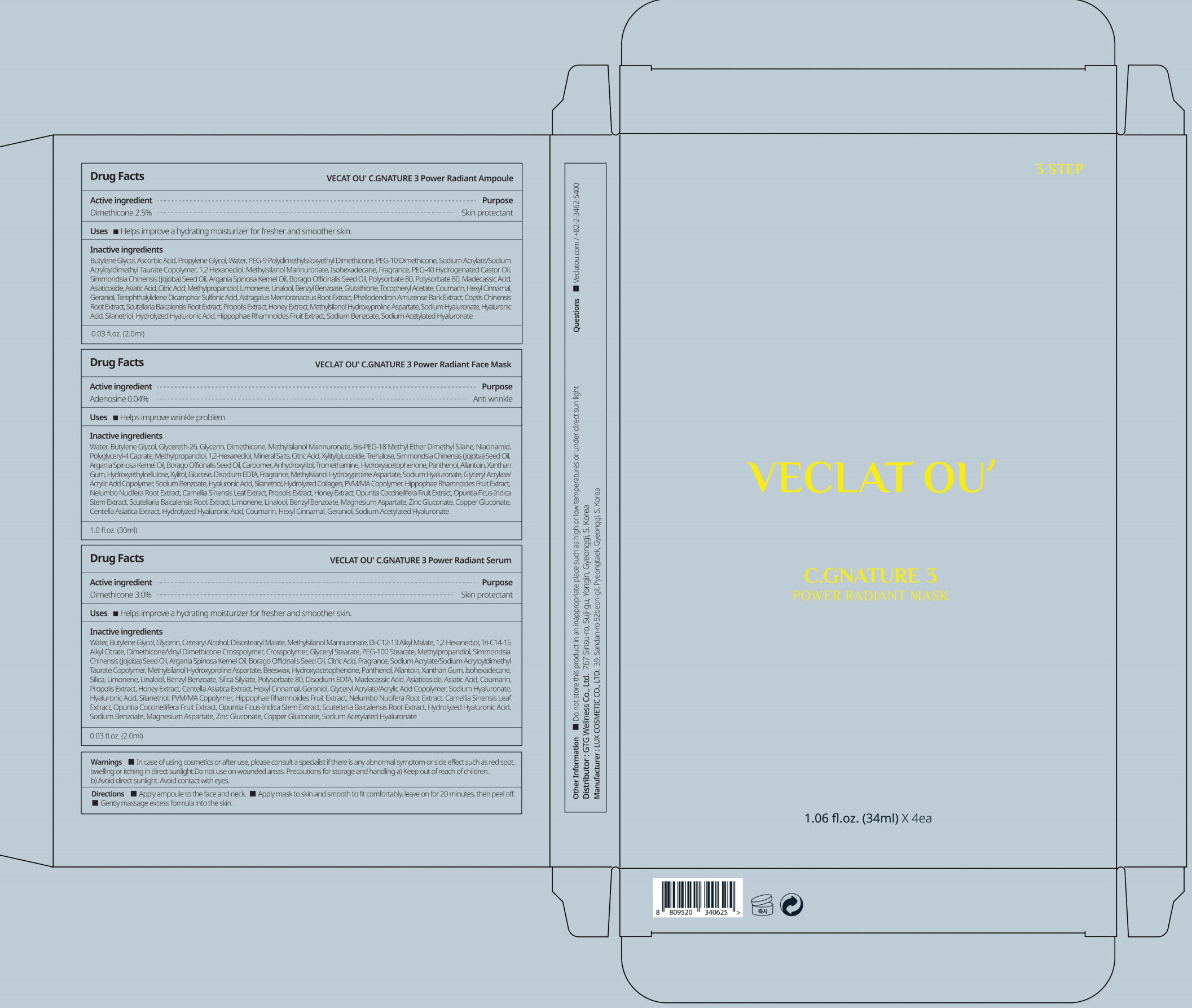 DRUG LABEL: VECLAT OU C.GNATURE 3 Power Radiant Face Mask
NDC: 71080-0027 | Form: PATCH
Manufacturer: GTG WELLNESS CO., LTD.
Category: otc | Type: HUMAN OTC DRUG LABEL
Date: 20211124

ACTIVE INGREDIENTS: Adenosine 0.04 g/100 mL
INACTIVE INGREDIENTS: Water; Butylene Glycol; Glycereth-26; Glycerin

ACTIVE INGREDIENT

Adenosine 0.04%

INACTIVE INGREDIENTS

Water, Butylene Glycol, Glycereth-26, Glycerin, Dimethicone, Methylsilanol Mannuronate, Bis-PEG-18 Methyl Ether Dimethyl Silane, Niacinamid, Polyglyceryl-4 Caprate, Methylpropandiol, 1,2-Hexanediol, Mineral Salts, Citric Acid, Xylitylglucoside, Trehalose, Simmondsia Chinensis (Jojoba) Seed Oil, Argania Spinosa Kernel Oil, Borago Officinalis Seed Oil, Carbomer, Anhydroxylitol, Tromethamine, Hydroxyacetophenone, Panthenol, Allantoin, Xanthan Gum, Hydroxyethylcellulose, Xylitol, Glucose, Disodium EDTA, Fragrance, Methylsilanol Hydroxyproline Aspartate, Sodium Hyaluronate, Glyceryl Acrylate/Acrylic Acid Copolymer, Sodium Benzoate, Hyaluronic Acid, Silanetriol, Hydrolyzed Collagen, PVM/MA Copolymer, Hippophae Rhamnoides Fruit Extract, Nelumbo Nucifera Root Extract, Camellia Sinensis Leaf Extract, Propolis Extract, Honey Extract, Opuntia Coccinellifera Fruit Extract, Opuntia Ficus-Indica Stem Extract, Scutellaria Baicalensis Root Extract, Limonene, Linalool, Benzyl Benzoate, Magnesium Aspartate, Zinc Gluconate, Copper Gluconate, Centella Asiatica Extract, Hydrolyzed Hyaluronic Acid, Coumarin, Hexyl Cinnamal, Geraniol, Sodium Acetylated Hyaluronate

PURPOSE

Anti wrinkle

WARNINGS

In case of using cosmetics or after use, please consult a specialist if there is any abnormal symptom or side effect such as red spot, swelling or itching in direct sunlight.
Do not use on wounded areas.
Precautions for storage and handling
a) Keep out of reach of children.
b) Avoid direct sunlight.
Avoid contact with eyes.

KEEP OUT OF REACH OF CHILDREN

Uses

■ Helps improve wrinkle problem

Directions

■ Apply ampoule to the face and neck.
■ Apply mask to skin and smooth to fit comfortably, leave on for 20 minutes, then peel off.
■ Apply serum to the entire face and neck.

Other information

■ Do not store this product in an inappropriate place such as high or low temperatures or under direct sun light

Questions

■ Veclatou.com / +82-2-3462-5400